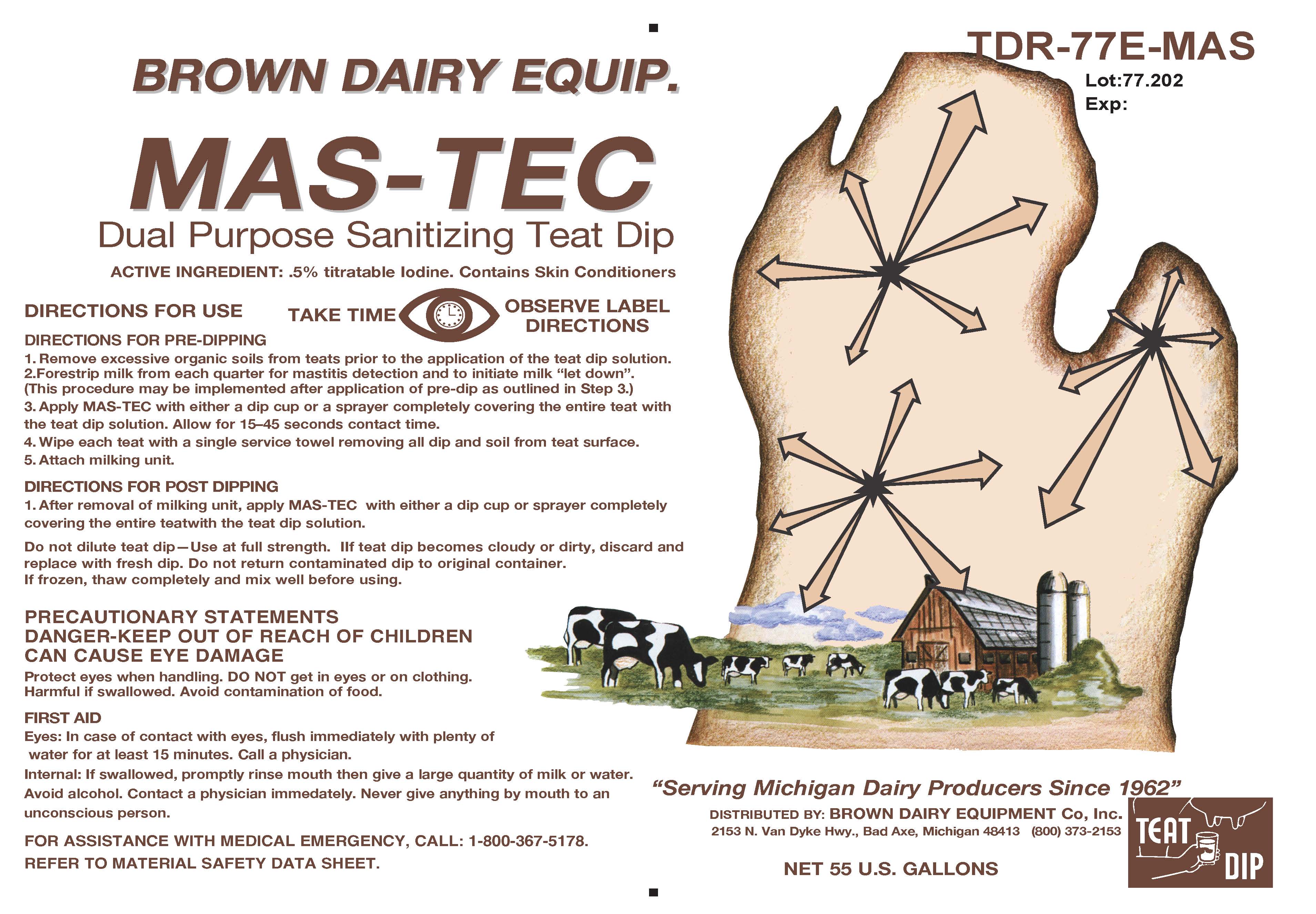 DRUG LABEL: MAS-TEC
NDC: 62897-777 | Form: SOLUTION
Manufacturer: Brown Dairy Equipment
Category: animal | Type: OTC ANIMAL DRUG LABEL
Date: 20211122

ACTIVE INGREDIENTS: IODINE 5 g/1 L
INACTIVE INGREDIENTS: SORBITOL; C12-15 PARETH-9; XANTHAN GUM; POVIDONE K30; SODIUM HYDROXIDE; PHOSPHORIC ACID; WATER

MAS-TEC
Dual Purpose Sanitizing Teat Dip

ACTIVE INGREDIENT: .5 % titratable Iodine

Contains Skin Conditioners

TAKE TIME

OBSERVE LABEL DIRECTIONS

INDICATIONS AND USAGE

DIRECTIONS FOR USE

DIRECTIONS FOR PRE-DIPPING

1. Remove excessive soils from teats prior to the application of the teat dip solution.
2. Forestrip milk from each quarter for mastitis detection and to initiate milk "let down". (This procedure may be implemented after application of pre-dip as outlined in Step 3.)
3. Apply MAS-TEC with either a dip cup or a sprayer completely covering the entire teat with the teat dip solution. Allow for 15-45 seconds contact time.
4. Wipe each teat with a single service towel removing all dip and soil from teat surface.
5. Attach milking unit.

DIRECTIONS FOR POST DIPPING

1. After removal of milking unit, apply MAS-TEC with either a dip cup or sprayer completely covering the entire teat with the teat dip solution.

WARNINGS

Do not dilute teat dip-Use at full strength.

If teat dip becomes cloudy or dirty, discard and replace with fresh dip.

Do not return contaminated dip to original container.

If frozen, thaw completely and mix will before using.

DANGER - KEEP OUT OF REACH OF CHILDREN

PRECAUTIONS

PRECAUTIONARY STATEMENTS

CAN CAUSE EYE DAMAGE

Protect eyes when handling. DO NOT get in eyes or on clothing.

Harmful if swallowed. Avoid contamination of food.

FIRST AID

Eyes: In case of contact with eyes, flush immediately with plenty of water for at least 15 minutes. Call a physician.

Internal: If swallowed, promptly rinse mouth then give a lage quantity of milk or water.

Avoid alcohol. Contact a physician immediately. Never give anything by mouth to an unconscious person.

FOR ASSISTANCE WITH MEDICAL EMERGENCY, CALL: 1-800-367-5178

REFER TO MATERIAL SAFETY DATA SHEET

DISTRIBUTED BY: BROWN DAIRY EQUIPMENT Co, Inc.

2153 N. Van Dyke Hwy., Bad Axe, Michigan 48413

(800) 373-2153

NET CONTENTS: U.S. GALLONS

Lot:

Exp: